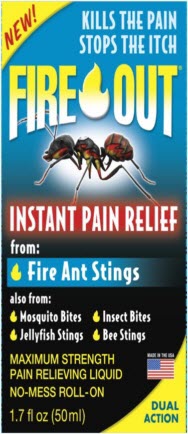 DRUG LABEL: Fire Out
NDC: 52412-300 | Form: SOLUTION
Manufacturer: Randob Ltd.
Category: otc | Type: HUMAN OTC DRUG LABEL
Date: 20190412

ACTIVE INGREDIENTS: BENZOCAINE 200 mg/1 mL; MENTHOL, UNSPECIFIED FORM 10 mg/1 mL
INACTIVE INGREDIENTS: FD&C BLUE NO. 1; ISOPROPYL ALCOHOL; PEG-8 LAURATE; WATER

Drug Facts

Active ingredient

Benzocaine USP 20%

Menthol USP 1%

Purpose

(for pain) Topical Anesthetic

(anti-itch) Antipruritic

Keep Out of Reach of Children

If swallowed get medical help or contact Poison Control Center right away.

Uses

- Temporarily relieves pain and itching of fire ant bites and stings, insect bites and stings, and minor skin irritation.

Warnings

- For external use only
- Do not apply over large areas of the body
- Avoid contact with eyes, mouth, and mucous membranes

Directions

Children under 2 yrs.

- Do not use
- Consult doctor

Adults and children 2 yrs. and older

- Clean area
- Apply to affected area as needed not more than 3 to 4 times a day.

Inactive Ingredients

FD&C Blue #1, Isopropyl Alcohol 15%, PEG-8 Laurate, Water.

Package/Label Principal Display Panel

NEW!

KILLS THE PAIN

STOPS THE ITCH

FIRE OUT™

INSTANT PAIN RELIEF

from:

Fire Ant Stings

also from:

Mosquito Bites Insect Bites
Jellyfish Stings Bee Stings

MAXIMUM STRENGTH

PAIN RELIEVING LIQUID

NO-MESS ROLL-ON

1.7 fl oz (50 ml)

MADE IN THE USA

DUAL ACTION